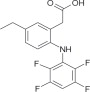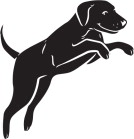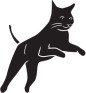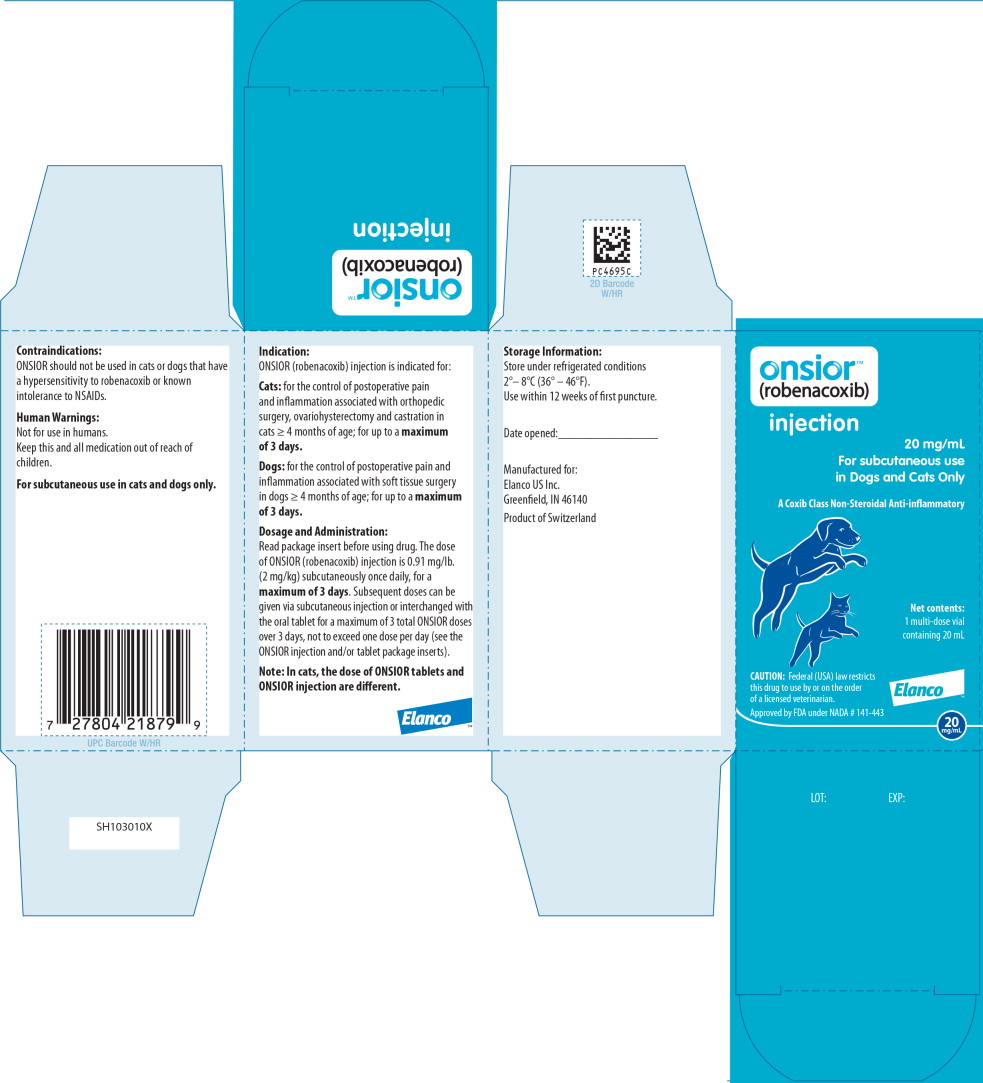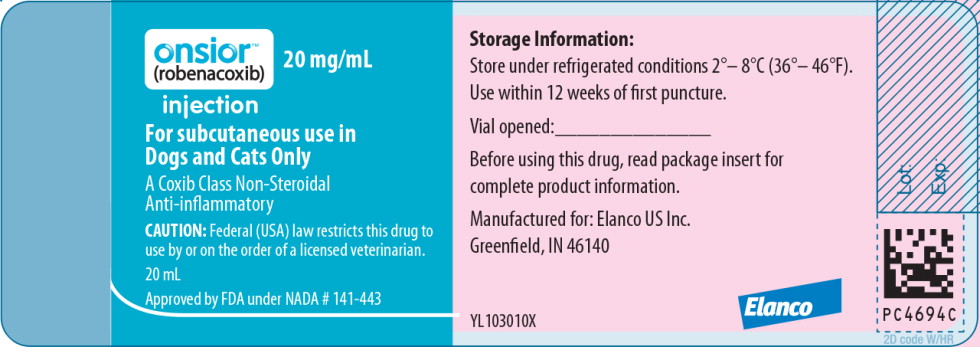 DRUG LABEL: Onsior
NDC: 58198-4886 | Form: INJECTION
Manufacturer: Elanco US Inc.
Category: animal | Type: PRESCRIPTION ANIMAL DRUG LABEL
Date: 20260105

ACTIVE INGREDIENTS: robenacoxib 20 mg/1 mL

Onsior™
(robenacoxib)

Injection
20 mg/mL injection
For Subcutaneous Use In Cats

Caution:

Federal (USA) law restricts this drug to use by or on the order of a licensed veterinarian.

Description:

ONSIOR (robenacoxib) injection is a non-narcotic, non-steroidal anti-inflammatory drug (NSAID) of the coxib class. Each mL of this clear sterile solution for injection contains 20 mg robenacoxib, 350 mg polyethylene glycol 400, 120 mg ethanol, 100 mg poloxamer 188, 1 mg sodium metabisulfite; citric acid and sodium hydroxide are used for pH adjustment. The molecular weight of robenacoxib is 327.28. The empirical formula is C16-H13-F4-NO2. Robenacoxib is [5-Ethyl-2-(2,3,5,6-tetrafluoro-phenylamino)-phenyl]acetic acid. The structural formula is:

Indication:

ONSIOR (robenacoxib) injection is indicated for the control of postoperative pain and inflammation associated with orthopedic surgery, ovariohysterectomy and castration in cats ≥ 4 months of age; for up to a maximum of 3 days.

Dosage and Administration:

Carefully consider the potential benefits and risks of ONSIOR and other treatment options before deciding to use ONSIOR (robenacoxib) injection. Use the lowest effective dose for the shortest duration consistent with individual response. It is recommended as good aseptic practice to clean stopper surface with isopropyl alcohol before and after each insertion of a needle.

The dose of ONSIOR (robenacoxib) injection is 0.91 mg/lb (2 mg/kg) subcutaneously once daily, for a maximum of 3 days.

Dosage Directions: For subcutaneous injection in cats ≥ 4 months of age; for up to a maximum of 3 days. To ensure accuracy of dosing, the use of a 1 mL graduated syringe is recommended. The first dose should be administered approximately 30 minutes prior to surgery, at the same time as the pre-anesthetic agents are given.

Subsequent doses can be given via subcutaneous injection, or interchanged with the oral tablet in cats ≥ 5.5 lbs and ≥ 4 months of age, for a maximum of 3 total ONSIOR doses over 3 days, not to exceed one dose per day (see Animal Safety and ONSIOR tablet product insert).

Note: In cats, the dose of ONSIOR tablets and ONSIOR injection are different.

Contraindications:

ONSIOR (robenacoxib) injection should not be used in cats that have a hypersensitivity to robenacoxib or known intolerance to NSAIDs.

Warnings:

Not for use in humans. Keep this and all medications out of reach of children.

Consult a physician in case of accidental ingestion or injection by humans. For subcutaneous use in cats and dogs (see reverse side for instructions for use in dogs).

All cats should undergo a thorough history and physical examination before the initiation of NSAID therapy. Appropriate laboratory tests should be conducted to establish hematological and serum biochemical baseline data prior to administration of an NSAID. Owners should be advised to observe for signs of potential drug toxicity (see Adverse Reactions and Animal Safety).

Do not administer ONSIOR injection or tablets in conjunction with any other oral or injectable NSAID or corticosteroid.

Precautions:

When using NSAIDS such as ONSIOR, the use of fluid therapy during surgery is recommended to decrease potential renal complications (see Adverse Reactions, Post-Approval Experience).

Appetite should be monitored in cats receiving ONSIOR.

Stop administration of ONSIOR if appetite decreases or if the cat becomes lethargic.

Inflammation at the injection site may be noted.

The use of ONSIOR has not been evaluated in cats younger than 4 months of age and less than 5.5 lbs, cats used for breeding, or in pregnant or lactating cats. Long-term use of the injectable has not been studied. Safety has not been demonstrated for IV or IM administration.

The use of ONSIOR in cats with cardiac disease has not been studied. ONSIOR has been shown to prolong the QT interval.

As a class, cyclo-oxygenase inhibitory NSAIDs may be associated with gastrointestinal, renal, and hepatic toxicity. Sensitivity to drug-associated adverse events varies with the individual patient. Cats that have experienced adverse reactions from one NSAID may experience adverse reactions from another NSAID. Patients at greatest risk for adverse events are those that are dehydrated, on concomitant diuretic therapy, or those with existing renal, cardiovascular, and/or hepatic dysfunction. Anesthetic drugs may affect renal perfusion; approach concomitant use of anesthetics and NSAIDs cautiously.

Appropriate monitoring procedures (including ECG, blood pressure, and temperature regulation) should be employed during all surgical procedures. The use of parenteral fluids during surgery is recommended to decrease potential renal complications when using NSAIDs perioperatively.

If additional pain medication is needed after a daily dose of ONSIOR, a non-NSAID/ non-corticosteroid class of analgesic may be necessary. Concurrent administration of potentially nephrotoxic drugs should be carefully approached and monitored. NSAIDs may inhibit prostaglandins which maintain normal homeostatic function. Such antiprostaglandin effects may result in clinically significant disease in patients with underlying or pre-existing disease that has not been previously diagnosed. NSAIDs possess the potential to produce gastrointestinal ulcerations and/or gastrointestinal perforations. Do not use ONSIOR concomitantly with other anti-inflammatory drugs, such as NSAIDs or corticosteroids. Consider appropriate washout times when switching from one NSAID to another or when switching from corticosteroid use to NSAID use. ONSIOR injection and ONSIOR tablets are safe to use interchangeably when given once a day for a maximum of 3 days in cats ≥ 4 months of age and ≥ 5.5 lbs. Note: In cats, the dose of ONSIOR tablets and ONSIOR injection are different.

The use of concomitantly protein-bound drugs with ONSIOR has not been studied in cats. Commonly used protein-bound drugs include cardiac, anticonvulsant and behavioral medications. The influence of concomitant drugs that may inhibit metabolism of ONSIOR has not been evaluated. Drug compatibility should be monitored in patients requiring adjunctive therapy. Concurrent medications used during the field study with ONSIOR included parasiticides, anesthetics, pre-anesthetic medications, and antibiotics.

The effect of cyclo-oxygenase inhibition and the potential for thromboembolic occurrence or a hypercoagulable state has not been evaluated. It is unknown whether cats with a history of hypersensitivity to ß lactam drugs will exhibit hypersensitivity to ONSIOR. Robenacoxib is poorly soluble in water and in acid solutions readily degrades to form γ-lactam. In cats, lactam is a metabolite of robenacoxib. Additionally, lactam is a degradation product that increases over the shelf-life of the solution. Neurologic signs have been associated with the use of ß lactam drugs; it is unknown if the lactam in robenacoxib may cause similar neurologic signs (see Animal Safety). Occurrences of skin lesions/urticaria, seizures, ataxia, and nystagmus have been associated with the use of ONSIOR.

Robenacoxib may prolong the QT interval; the associated risk of developing ventricular arrhythmia is unknown. The use of robenacoxib with other drugs shown to prolong the QT interval is not recommended. Commonly used drugs that prolong the QT interval include antihistamines, prokinetic, and certain anesthetic drugs. ONSIOR (robenacoxib) injection contains sodium metabisulfite. ONSIOR (robenacoxib) injection should not be used in patients with sulfite hypersensitivity. As a class, it is unknown if the use of NSAIDs in asthmatic cats can cause acute asthmatic exacerbations, as seen in some humans.

Adverse Reactions:

The controlled field study (see Effectiveness) included a total of 349 healthy male and female cats in the field safety analysis. ONSIOR (robenacoxib) injection treated cats represented 7 breeds, 4 months to 7 years old, weighing 5.5-13.2 lbs. The following table shows the number of cats exhibiting each observation.

Adverse Reactions in the Postoperative Pain Field Study
Adverse Reaction* | ONSIOR N = 174** | Control (0.9% physiologic saline) N = 175
Incision site infection, dehiscence | 9 | 0
Increased incision site bleeding | 6 | 4
Vomiting | 5 | 0
Decreased appetite | 4 | 3
Lethargy (after day of surgery) | 4 | 2
UTI | 2 | 0
Coughing | 1 | 0
Fever | 1 | 0
Semiconscious*** | 1 | 0
Soft stool, diarrhea | 0 | 2
*Cats may have experienced more than one type or occurrence of an event during the study.
**One ONSIOR cat suffered an anesthetic-related death.
***Semiconscious cat fully recovered.

The most commonly reported adverse reactions in cats treated with ONSIOR (robenacoxib) injection were infected incision sites, increased incision site bleeding, vomiting, inappetence, and lethargy. Changes in the clinical pathology values were not considered clinically significant.

An additional study was conducted in client-owned cats to evaluate ONSIOR (robenacoxib) injection at a dose of 2 mg/kg administered once daily for the control of postoperative pain and inflammation associated with an onychectomy (forelimbs only) and OVH or castration. The study was a masked, negative controlled, multi-center field study in which 187 cats were enrolled in a 2:1 ratio into two groups (127 cats treated with robenacoxib injection and 60 cats treated with saline).

Adverse Reactions from Additional Field Study
Adverse Reaction* | ONSIOR N = 127 | Control (0.9% physiologic saline N = 60
Surgical or venipuncture site bleeding | 9 | 3
Leukocytosis | 9 | 2
Fever | 8 | 11
Lethargy (after day of surgery) | 7 | 0
Vomiting | 6 | 0
Anorexia/ decreased appetite | 6 | 3
Infected/drainage surgical site(s), infection | 5 | 2
Dehiscence | 1 | 0
Diarrhea | 1 | 3
Bloody stool | 1 | 0
Hypersalivation | 1 | 2
UTI | 0 | 1
*Cats may have experienced more than one type or occurrence of an event during the study.

The mean WBC count in the ONSIOR group was 13.8 ± 5.64 10^3/μL (ranging from 4.4 – 36.8) and the mean WBC count in the control group was 12.7 ± 5.41 10^3/μL (with values ranging from 2.9 – 30.1) at the end of the study. There were 6 ONSIOR cases with elevated ALT post-treatment compared to 1 control case. There were 4 ONSIOR cases with elevated AST post-treatment compared to 1 control case.

The most commonly reported adverse reactions in cats treated with ONSIOR were increased incision site bleeding, leukocytosis, fever, inappetence, infected incision sites, vomiting, and lethargy.

The results of the field study demonstrate that ONSIOR injection, when administered for a maximum of 3 days, is well-tolerated for the control of postoperative pain associated with onychectomy, ovariohysterectomy, and castration in cats.

Post Approval Experience (2015):

The following adverse events are based on voluntary, post approval reporting. Not all adverse events are reported to FDA/CVM. It is not always possible to reliably estimate the adverse event frequency or establish a causal relationship to product exposure using these data.

The signs reported are listed in decreasing order of reporting frequency for ONSIOR tablets in cats:

Anorexia, depression/lethargy, vomiting, elevated BUN, elevated creatinine, renal insufficiency/ failure, diarrhea, weight loss, dehydration.

In some cases, death has been reported. Some of these cases involved patients that developed renal failure/renal insufficiency.

To report suspected adverse drug events and for technical assistance, contact Elanco US Inc. at 1-888-545-5973.

For additional information about adverse drug experience reporting for animal drugs, contact FDA at 1-888-FDA-VETS or online at http://www.fda.gov/reportanimalae

Information for Cat Owners:

ONSIOR, like other drugs of its class, is not free from adverse reactions. Owners should be advised of the potential for adverse reactions and be informed of the clinical signs associated with drug intolerance.

Adverse reactions may include vomiting, diarrhea, decreased appetite, dark or tarry stools, increased water consumption, increased urination, anemia, yellowing of gums, skin or white of the eye due to jaundice, lethargy, incoordination, seizure, or behavioral changes. Serious adverse reactions associated with this drug class can occur without warning and result in death (see Warnings and Adverse Reactions). Owners should be advised to contact their veterinarian immediately if signs of intolerance are observed. The vast majority of patients with drug related adverse reactions have recovered when the signs are recognized, the drug is withdrawn, and veterinary care, if appropriate, is initiated.

Clinical Pharmacology:

In an inflammation model in cats, robenacoxib had analgesic, anti-inflammatory and anti-pyretic actions with a rapid onset of action (0.5 h). ^1 In an in vitro whole blood assay in cats, robenacoxib demonstrated selective COX-2 inhibition. ^2 The clinical relevance of this data has not been shown. Robenacoxib is an analog of diclofenac.

Absorption

Peak blood concentrations of robenacoxib are attained rapidly after subcutaneous injection in cats. After a dosage of 2 mg/kg, a Tmax of 1 hour, a Cmax of 1464 ng/ml and an AUC(0-inf) of 3128 ng.h/ml is obtained. The injection has a systemic bioavailability of 69%, which is higher than that observed after an equivalent oral dose. A slightly less than dose proportional increase in exposure was observed with an increase in dose (a 2X dose resulted in a 1.4X increase in drug exposure; a 3X increase in dose resulted in a 2.3X increase in drug exposure).

Distribution

Robenacoxib has a relatively small volume of distribution (mean Vss = 190 ml/kg) and is highly bound to plasma proteins (>99%). Robenacoxib persists longer in the inflammatory exudate of a tissue cage model than in blood. The median robenacoxib elimination half-life in exudate was about 27 hours versus 2.5 hours for blood.

Metabolism

Robenacoxib is extensively metabolized by the liver in cats. Apart from one lactam metabolite, the identity of other metabolites is not known.

Elimination

Robenacoxib is rapidly cleared from blood (mean clearance [CL] = 0.44 L/kg/h) with an elimination mean half-life (t1/2) of 1.1 hours after intravenous administration. After subcutaneous administration, the terminal half-life was 1.1 hour (range of estimated values was 0.9 hour to 1.6 hours). Repeated subcutaneous administration at dosages of 2-20 mg/kg produced no change in the blood profile, with neither bioaccumulation of robenacoxib nor enzyme induction. Elimination occurs predominantly through the biliary route (fecal and urinary excretion are 60 and 16.5% respectively). The pharmacokinetics of robenacoxib injection does not differ between male and female.

Animal Safety:

3-day Target Animal Safety Study: In a laboratory study, ONSIOR (robenacoxib) injection was administered subcutaneously once daily for 3 days at 5 times the labeled dose (5X = 10 mg/kg). Treatment was associated with vomiting, soft feces/diarrhea, and injection site swelling which disappeared within 72 hours following injection. Histologically, minimal to slight inflammatory cell infiltration in the subcutaneous tissue underlying the injection site was noted in most treated and saline-control cats. Minimal to moderate, locally extensive subcutaneous muscle necrosis and signs of muscle regeneration were seen in 35/37 biopsies of the injection sites in treated cats and in none of the control cat biopsies. Several treated cats had clinically significant elevations in creatine kinase (CK) levels compared to the control cats.

37-Day Interchangeable Use Study: ONSIOR was administered orally (6 mg tablets) and subcutaneously (20 mg/mL solution) to 4-month old healthy cats at 0, 1, 2, and 3 times the labeled doses (1X = 2.4 mg/kg/day orally based on the inherent tablet dose band or 2.0 mg/kg/day subcutaneously). Interchangeable use was evaluated by alternating three 7-day oral tablet/3-day subcutaneous injection cycles followed by one final 7-day oral tablet dosing cycle. All cats survived until study termination. Findings included: elevated creatine kinase levels on Days 13 and 37, soft stools, histologic observation of a minimal oral (tongue) ulceration in a 1X cat, injection site edema for up to 120 hours prior to resolution, and a prolonged QT interval in treated cats as compared to the controls on Day 36. There was a dose dependent and statistically significant increase in the QT interval at all three ONSIOR tablets/ONSIOR injection treatment levels. It is unknown if the increased QT interval suggests an elevated risk of ventricular arrhythmia or torsade de pointes in cats. In addition, a longer PR interval was noted in 1X group females on Day 36 compared to the controls. One 2X cat vomited twice during the last 2 dosing days. Histologically, the injection sites had minimal or mild, subacute/chronic inflammation. Inflammation at the injection sites was observed in both treated and control animals with a greater frequency in the higher dose groups than in the control and 1X groups. Dose-normalized AUC and concentration levels were higher following the oral route than the subcutaneous route. There was no significant accumulation following once daily administration. One 2X-treated cat had a 7-fold increase in buccal mucosal bleeding time (BMBT) during the treatment period compared to the pre-treatment value.

Preliminary 37-Day Interchangeable Use Study: ONSIOR was administered orally

(6 mg tablets) and subcutaneously (20 mg/mL solution) to 4-month old cats at 0, 1, and 5 times the labeled doses (1X = 2.4 mg/kg/day orally based on the inherent tablet dose band or 2.0 mg/kg/day subcutaneously). Interchangeable use was evaluated by alternating three 7-day oral tablet/3-day subcutaneous injection cycles followed by one final 7-day oral tablet dosing cycle. Clinical findings included: scabs and sores at the injection sites of one 1X female and two 5X females, and injection site edema noted more frequently in treated cats. Injection site changes were characterized as minimal to moderate granulomatous inflammation, minimal to moderate fibroplasia/fibrosis, and minimal myofiber regeneration of the panniculus carnosus. In one 1X female, moderate necrosis of a blood vessel was noted within the granulomatous inflammation. Minimal myofiber regeneration was observed in the underlying skeletal muscle in three out of four 5X males.

A red depressed area on the upper lip of one 5X cat correlated histologically with a minimal ulcer. Creatinine was significantly increased in 5X cats compared to the controls. Urine specific gravities remained within normal limits for all 5X cats, and blood urea nitrogen (BUN) values remained within normal limits for all study animals. Histologically, renal changes included bilateral or unilateral minimal to moderate vacuolation and bilateral or unilateral minimal to mild degeneration of proximal tubules were observed in three 5X males. Two 5X males had mineralized foci in the epithelium covering the papilla.

One 5X female had a brief episode of ataxia and lethargy on Day 16. This cat was subsequently noted to be dehydrated and constipated, requiring veterinary intervention with subcutaneous fluid therapy and nutritional supplementation. This cat had the greatest QT increase on ECG evaluation.

Effectiveness:

Effectiveness was demonstrated using ONSIOR (robenacoxib) injection in a masked, placebo-controlled, multi-site field study involving client-owned cats. In this study, 349 cats presenting for ovariohysterectomy or castration in conjunction with an onychectomy (forelimbs only) were randomly administered ONSIOR injection or saline. Drug was administered approximately 30 minutes prior to surgery along with pre-anesthetic medications and continued once daily for two additional treatments. Effectiveness was evaluated in 348 cats (173 treated and 175 controls) and field safety was evaluated in 349 cats. A statistically significant difference in the proportion of treatment successes in the ONSIOR injection treatment group (83.5%) compared to the control group (61.9%) was observed. Statistically significant differences for pain elicited on palpation at the spay or castration incision site, paw pain, behavior following social interaction and from a distance, posture score and overall pain at various postsurgical time points were also observed. The results of the field study demonstrate that ONSIOR (robenacoxib) injection when administered for a maximum of 3 days is effective and well-tolerated for the control of postoperative pain associated with onychectomy, ovariohysterectomy, and castration in cats.

How Supplied:

ONSIOR (robenacoxib) injection is available as a 20 mg/mL solution in a 20 mL multidose vial.

Storage Conditions:

Store under refrigerated conditions 2°– 8°C (36° – 46°F). Use within 12 weeks of first puncture.

Manufactured for: | Elanco US, Inc.
 | Greenfield, IN 46140

References:

^1Giraudel, J.M., King J.N., Jeunesse, E.C., Lees, P. & Toutain, P.L. (2008). Use of a pharmacokinetic/pharmacodynamic approach in the cat to determine a dosage regimen for the COX-2 selective drug robenacoxib. J Vet Pharmacol Ther 2009;32:18-30.

^2Giraudel, J.M., Toutain, P.L., King J.N., & Lees, P. Differential inhibition of cyclooxygenase isoenzymes in the cat by the COX-2 selective drug robenacoxib. J Vet Pharmacol Ther 2009;32:31-40.

Approved by FDA under NADA # 141-443

Onsior, Elanco and the diagonal bar logo are trademarks of Elanco or its affiliates.

Revised: July 2020
PA103010X
Elanco™

Onsior™
(robenacoxib)

Injection

20 mg/mL injection

For Subcutaneous Use in Dogs

Caution:

Federal (USA) law restricts this drug to use by or on the order of a licensed veterinarian. Description:

ONSIOR (robenacoxib) injection is a non-narcotic, non-steroidal anti-inflammatory drug (NSAID) of the coxib class. Each mL of this clear sterile solution for injection contains 20 mg robenacoxib, 350 mg polyethylene glycol 400, 120 mg ethanol, 100 mg poloxamer 188, 1 mg sodium metabisulfite; citric acid and sodium hydroxide are used for pH adjustment.The molecular weight of robenacoxib is 327.28. The empirical formula is C16-H13-F4-NO2. Robenacoxib is [5-Ethyl-2-(2,3,5,6-tetrafluoro-phenylamino)-phenyl]-acetic acid. The structural formula is:

Indication:

ONSIOR (robenacoxib) injection is indicated for the control of postoperative pain and inflammation associated with soft tissue surgery in dogs ≥ 4 months of age; for up to a maximum of 3 days.

Dosage and Administration:

Carefully consider the potential benefits and risks of ONSIOR and other treatment options before deciding to use ONSIOR (robenacoxib) injection. Use the lowest effective dose for the shortest duration consistent with individual response. It is recommended as good aseptic practice to clean stopper surface with isopropyl alcohol before and after each insertion of a needle.

The dose of ONSIOR (robenacoxib) injection is 0.91 mg/lb (2 mg/kg) subcutaneously once daily, for a maximum of 3 days (See Warnings, Precautions and Adverse Reactions). Dosage Directions: For subcutaneous injection in dogs ≥ 4 months of age; for up to a maximum of 3 days. The first dose should be administered approximately 45 minutes prior to surgery, at the same time as the pre-anesthetic agents are given.

Subsequent doses can be given via subcutaneous injection, or interchanged with the oral tablet in dogs ≥ 5.5 lbs and ≥ 4 months of age, for a maximum of 3 total ONSIOR doses over 3 days, not to exceed one dose per day (see Animal Safety and ONSIOR tablet product insert). If subsequent doses are given by subcutaneous injection, different sites for each injection should be used (See Adverse Reactions).

Contraindications:

ONSIOR (robenacoxib) should not be used in dogs that have a hypersensitivity to robenacoxib or known intolerance to NSAIDs.

Warnings:

Not for use in humans. Keep this and all medications out of reach of children. Consult a physician in case of accidental exposure to humans. For subcutaneous use in dogs and cats only. See reverse side for instructions for use in cats.

Do not administer ONSIOR injection or tablets in conjunction with any other oral or injectable NSAID or corticosteroid.

Do not use for more than 3 days. Serious adverse events have been reported, including hepatopathy, with the long term use (28 day study) of ONSIOR tablets in dogs (See Adverse Reactions). Safety not demonstrated for longer than 3 days.

All dogs should undergo a thorough history and physical examination before the initiation of NSAID therapy. Appropriate laboratory tests should be conducted to establish hematological and serum biochemical baseline data prior to administration of an NSAID. Owners should be advised to observe for signs of potential drug toxicity (see Adverse Reactions and Animal Safety).

Precautions:

Monitor dogs post-injection for reactions. Injection site reactions and anaphylactic reactions have been associated with the use of ONSIOR injection (See Adverse Reactions). Stop administration of ONSIOR if the dog experiences inappetence, vomiting or lethargy.

The safe use of ONSIOR has not been evaluated in dogs younger than 4 months of age, dogs used for breeding, or in pregnant or lactating dogs. Safety has not been demonstrated for intravenous or intramuscular administration of ONSIOR injection.

As a class, cyclo-oxygenase inhibitory NSAIDS may be associated with gastrointestinal, renal, and hepatic toxicity. Sensitivity to drug-associated adverse events varies with the individual patient. Dogs that have experienced adverse reactions from one NSAID may experience adverse reactions from another NSAID. Patients at greatest risk for adverse events are those that are dehydrated, on concomitant diuretic therapy, or those with existing renal, cardiovascular, and/or hepatic dysfunction. Anesthetic drugs may affect renal perfusion; approach concomitant use of anesthetics and NSAIDS cautiously. Appropriate monitoring procedures (including ECG, blood pressure, and temperature regulation) should be employed during all surgical procedures. The use of parenteral fluids during surgery is recommended to decrease potential renal complications when using NSAIDS perioperatively.

If additional pain medication is needed after a daily dose of ONSIOR, a non-NSAID/ non- corticosteroid class of analgesic may be necessary. Concurrent administration of potentially nephrotoxic drugs should be carefully approached and monitored. NSAIDs may inhibit prostaglandins which maintain normal homeostatic function. Such antiprostaglandin effects may result in clinically significant disease in patients with underlying or pre-existing disease that has not been previously diagnosed. NSAIDs possess the potential to produce gastrointestinal ulcerations and/or gastrointestinal perforations. Do not use ONSIOR concomitantly with other anti-inflammatory drugs, such as NSAIDs or corticosteroids. Consider appropriate washout times when switching from one NSAID to another or when switching from corticosteroid use to NSAID use. ONSIOR injection and ONSIOR tablets are safe to use interchangeably when given once a day for a maximum of 3 days in dogs ≥ 4 months of age and ≥ 5.5 lbs.

The use of concomitantly protein-bound drugs with ONSIOR has not been studied in dogs. Commonly used protein-bound drugs include cardiac, anticonvulsant, and behavioral medications. The influence of concomitant drugs that may inhibit metabolism of ONSIOR has not been evaluated. Drug compatibility should be monitored in patients requiring adjunctive therapy. Concurrent medications used during the field study with ONSIOR included parasiticides, anesthetics, pre-anesthetic medications, and antibiotics.

It is unknown whether dogs with a history of hypersensitivity to ß lactam drugs will exhibit hypersensitivity to ONSIOR. Robenacoxib is poorly soluble in water and in acid solutions readily degrades to form γ-lactam. In dogs, lactam is a minor metabolite of robenacoxib. Additionally, lactam is a degradation product that increases over the shelf life of the solution. Neurologic signs have been associated with the use of ß lactam drugs; it is unknown if the lactam produced by robenacoxib may cause similar neurologic signs.

ONSIOR (robenacoxib) injection contains sodium metabisulfite. ONSIOR (robenacoxib) injection should not be used in patients with sulfite hypersensitivity. A sulfite may cause allergic-type reactions including anaphylaxis.

Adverse Reactions:

In a controlled field study (See Effectiveness), a total of 317 male and female dogs representing various breeds were included in the field safety analysis. ONSIOR-treated dogs ranged in age from 6 months to 15 years and weighed between 2.5 and 53.8 kg. The following table shows the number of dogs exhibiting each observation.

Table 1: Adverse reactions reported in the soft tissue surgery field study.
Adverse Reaction* | ONSIOR (robenacoxib) injection N = 159 | Placebo (0.9% NaCl) N = 158
Pain on injection** | 18 | 8
Diarrhea | 15 | 8
Vomiting | 10 | 6
Bradycardia | 6 | 1
Decreased appetite | 5 | 2
Hypotension | 2 | 0
Facial edema, hypersensitivity | 1 | 0
Increased incisional bleeding | 1 | 0
* Dogs may have experienced more than one type or occurrence of an event during the study.
**Most often occurred as a single event.

Pain on injection, diarrhea and vomiting were the most commonly reported adverse reactions.

Occurrences of hepatopathy, ataxia, skin lesions/urticaria, and anaphylaxis have been associated with the use of ONSIOR. In a month-long pilot study, 3 dogs that received ONSIOR developed hepatic toxicity. Two of these dogs were euthanized and a third dog recovered after prolonged hospitalization and supportive therapy. In foreign market experience, elevated liver enzymes, hepatic necrosis and death have been associated with the long term use of robenacoxib in dogs. Occurrences of liver failure, hepatitis, and cholangiohepatitis have been reported. In two other field studies, bradycardia, 2nd degree heart block in four dogs, and ventricular arrhythmia in one dog were noted in anesthetized dogs treated with ONSIOR injection.

Injection site reactions (edema, necrosis, and abscesses), and anaphylactic reactions (panting, drooling, shock, pallor, dyspnea, tachypnea, ataxia) have been associated with the use of ONSIOR injection.

For technical assistance or to report suspected adverse drug events, contact Elanco US Inc. at 1-888-545-5973. For additional information about adverse drug experience reporting for animal drugs, contact FDA at 1-888-FDA-VETS or http://www.fda.gov/reportanimalae

Information for Dog Owners:

ONSIOR, like other drugs of its class, is not free from adverse reactions. Owners should be advised of the potential for adverse reactions and be informed of the clinical signs associated with drug intolerance. Adverse reactions may include vomiting, diarrhea, decreased appetite, dark or tarry stools, increased water consumption, increased urination, anemia, yellowing of gums, skin or whites of the eye due to jaundice, lethargy, incoordination, seizure, or behavioral changes. Serious adverse reactions associated with this drug class can occur without warning and in some cases result in death (see Warnings and Adverse Reactions). Owners should be advised to discontinue ONSIOR therapy and contact their veterinarian immediately if signs of intolerance are observed. The vast majority of patients with drug related adverse reactions have recovered when the signs are recognized, the drug is withdrawn, and veterinary care, if appropriate, is initiated.

Clinical Pharmacology:

Robenacoxib is a non-steroidal anti-inflammatory drug (NSAID) of the coxib class. Repeated subcutaneous administration is not associated with a bioaccumulation of robenacoxib. Although the bioaccumulation of robenacoxib metabolites has not been tested, radiolabeled studies suggest that the various unidentified metabolites are associated with a markedly longer elimination half-life (approximately 22 hours) as compared to that of the parent molecule. The activity of these metabolites has not been evaluated. The pharmacokinetics of robenacoxib injection does not differ between male and female dogs, and is linear over the range of 0.25-4 mg/kg in dogs.

Absorption

Peak blood concentrations of robenacoxib are attained rapidly after subcutaneous injection in dogs. After a dosage of 2 mg/kg, peak concentrations are generally achieved within 1-2 hours post-dose. After subcutaneous administration of 1 mg/kg to dogs, systemic bioavailability ranged from 67% to 100% (average = 89%).

Distribution

Robenacoxib has a relatively small volume of distribution (Vss of 174 to 336 mL/kg, average = 240 mL/kg), which is consistent with a drug that is extensively bound to plasma proteins. Based upon in vitro canine plasma samples, robenacoxib is approximately 98% bound to plasma proteins when spiked at concentrations ranging from 200 – 2000 ng/mL. The corresponding canine in vitro whole blood-plasma ratio in artificially spiked blood was 0.44.

Biotransformation

Robenacoxib is extensively metabolized by the liver in dogs. Apart from one lactam metabolite, the identity of other metabolites is not known in dogs. Robenacoxib is excreted predominately via the biliary route in dogs (approximately 65 %); therefore, the majority of the absorbed dose (parent drug and metabolites) is eliminated in the feces. The remainder of the administered dose is eliminated in urine via the kidneys.

Elimination

After intravenous administration to normal healthy dogs, robenacoxib is rapidly cleared from blood (CL of 0.61 to 1.13 L/kg/h, average = 0.81 L/kg/hr) with an elimination half-life ranging from 0.41 to 1.07 hrs. After subcutaneous administration to normal healthy dogs, the terminal half-life from blood was within 1 – 4 hrs.

Animal Safety:

88-Day Interchangeable Use Study: In an 88-day laboratory interchangeable use study, 4-month old healthy mongrel dogs (4 sex/dose) were administered three 20 day cycles (separated by a 14-day washout) of alternating regimens of ONSIOR tablets and ONSIOR injection. Each cycle included a schedule of 7 days once daily oral tablet administration (0, 2, 4, or 6 mg/kg/day; Groups 1, 2, 3, and 4, respectively), 3 days of once daily oral administration (0, 4, 8, or 12 mg/kg/day; Groups 1, 2, 3, and 4, respectively), 3 days of once daily subcutaneous injection (0, 4, 8, or 12 mg/kg/day; Groups 1, 2, 3, and 4, respectively), and then 7 days once daily oral administration (0, 2, 4, or 6 mg/kg/day; Groups 1, 2, 3, and 4, respectively). The negative control group (Group 1) received empty gelatin capsules or saline injection.

All mongrels were in good health through study termination. Injection site reactions, including skin thickening, ulceration, or granulation, occurred in dogs in all groups in a dose-dependent manner, including one control dog. Histologically, there was minimal to severe subcutaneous necrosis, degeneration, and/or fibrosis with occasional myonecrosis of the underlying panniculus muscle. On gross pathology, one dog in Group 2 had discoloration throughout the entire duodenal, jejunal, and ileal mucosa, as well as multiple mucosal discolorations in the stomach, with no corresponding histopathology findings, except for a jejunal ulcer with minimal inflammation. Another dog in Group 2 had stomach, duodenal and jejunal mucosal discoloration with no corresponding histopathology findings. One Group 3 dog had multiple mucosal discoloration in the stomach and duodenum with no histopathology findings; and microscopic minimal cecal hemorrhage with microscopic cecal inflammation. This dog also vomited on 2 days. Another dog in Group 3 had discoloration grossly along the entire duodenal and jejunal mucosa with no correlating histopathology findings; a single mucosal discoloration in the stomach with no histopathology findings, and slight duodenal congestion microscopically. This dog vomited on 3 study days. Microscopic cecal inflammation was noted in one Group 4 dog. There were no gastrointestinal findings noted in the control group. Treated male dogs exhibited an increased number and severity of lymphocyte depletion within the thymus compared to the controls.

3-Day Target Animal Safety Study: Injection site tolerance was evaluated in 5-7.5 year old, healthy Beagles. Subcutaneous administration of ONSIOR 20 mg/mL injection at 0 (saline), 2 mg/kg (1X), or 10 mg/kg (5X) once a day for 3 days (4/sex/dose) resulted in transient, fluid-filled, swellings which resolved within 72 hours. Histologically, ONSIOR-injected sites had minimal to slight subcutaneous inflammatory cell infiltration in the subcutis and regenerating, minimal to mild acute myonecrosis at 2 mg/kg and 10 mg/kg.

16-Day Target Animal Safety Study: After ONSIOR administration intravenously (IV) at 0 (saline), 2 mg/kg (1X) and 4 mg/kg (2X), and subcutaneously (SC) at 2 mg/kg (at least 72 hours apart) to healthy Beagles (4/sex; 1.5 - 3 years old), there were no effects on arterial blood pressure, heart rate, or cardiac conduction times during 8-hours of postdosing for cardiovascular telemetric measurements. No arrhythmia attributable to the test article was observed. Two dogs vomited after IV administrations at 4 mg/kg.

Effectiveness:

Effectiveness was demonstrated using ONSIOR (robenacoxib) injection in a masked, placebo-controlled, multi-site field study in which 317 client-owned dogs presenting for soft tissue surgery were randomized to receive ONSIOR injection or placebo. Drug was administered approximately 45 minutes prior to surgery, along with pre-anesthetic medications, and continued once daily for two additional treatments. Effectiveness was evaluated in 303 dogs and field safety was evaluated in 317 dogs. A statistically significant difference (p-value = 0.0055) was observed in the proportion of treatment successes in the ONSIOR injection treatment group (108/151; 73.7%) compared to the placebo group (85/152; 58.1%). Forty three of 151 dogs in the ONSIOR injection group and 67 of 152 dogs in the placebo group were treatment failures. Statistically significant differences in reductions in Response to Touch scores (p = 0.0013) and Posture/Activity (p = 0.0466) were observed in the ONSIOR injection group relative to the placebo group. The results of the field study demonstrate that subcutaneous administration of ONSIOR (robenacoxib) injection, when administered for a maximum of 3 days, is effective and well-tolerated for the control of postoperative pain associated with soft tissue surgery in dogs.

How Supplied:

ONSIOR (robenacoxib) injection is available as a 20 mg/mL solution in a 20 mL multidose vial.

Storage Conditions:

Store under refrigerated conditions 2° - 8°C (36° - 46°F).

Use within 12 weeks of first puncture.

Manufactured for: Elanco US Inc. Greenfield, IN 46140

Approved by FDA under NADA # 141-443
Onsior, Elanco and the diagonal bar logo are trademarks of Elanco or its affiliates.
Revised: July 2020
PA103010X

Principal Display Panel – Carton Label

onsior™

(robenacoxib)

injection

20 mg/mL

For subcutaneous use
in Dogs and Cats Only

A Coxib Class Non-Steroidal Anti-inflammatory

Net contents:

1 multi-dose vial

containing 20 mL

CAUTION: Federal (USA) law restricts
this drug to use by or on the order
of a licensed veterinarian.

NADA 141-443, Approved by FDA

Elanco™

20 mg/mL

Principal Display Panel – 20 mg Vial Label

onsior

(robenacoxib)

injection

20 mg/mL

For subcutaneous use in
Dogs and Cats Only

A Coxib Class Non-Steroidal

Anti-inflammatory

CAUTION: Federal (USA) law restricts this drug to
use by or on the order of a licensed veterinarian.

20 mL

NADA 141-443, Approved by FDA.